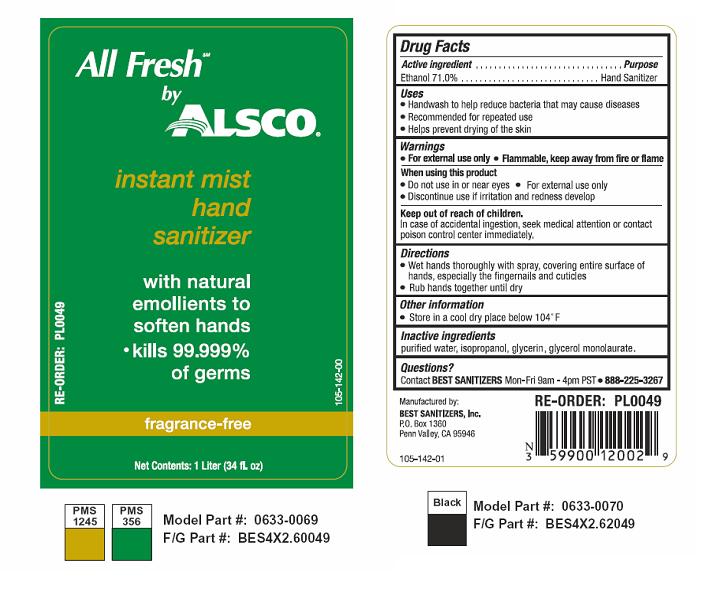 DRUG LABEL: All Fresh by Alsco Instant Mist Hand Sanitizer
NDC: 59900-120 | Form: LIQUID
Manufacturer: Best Sanitizers, Inc
Category: otc | Type: HUMAN OTC DRUG LABEL
Date: 20100305

ACTIVE INGREDIENTS: Ethanol 710 g/1000 mL

Drug Facts

Active Ingredient

Ethanol 71.0%

Purpose

Hand Sanitizer

Uses

- Handwash to help reduce bacteria that may cause disease
- Recommended for repeated use
- Helps to prevent drying of the skin

Warnings

- For external use only
- Flammable, keep away from fire or flame

When Using this product

- Do not use in or near eyes
- For external use only
- Discontinue use if irritation and redness develop

Keep out of reach of children

In case of accidental ingestion, seek medical attention or contact a poison control center immediately.

Directions

- Wet hands thoroughly with spray, covering entire surface of hands, especially the fingernails and cuticles
- Rub hands together until dry

Other information

- Store in a cool dry place below 104° F

Inactive ingredients

purified water, isopropanol, glycerin, glycerol monolaurate

Questions?

Contact Best Sanitizers Mon-Fri 9am-4pm PST at 888-225-3267

Principal Display Panel

NDC 59900-120-01

NDC 59900-120-02

NDC 59900-120-03

All Fresh™ by Alsoco
Instant Mist Hand Sanitizer